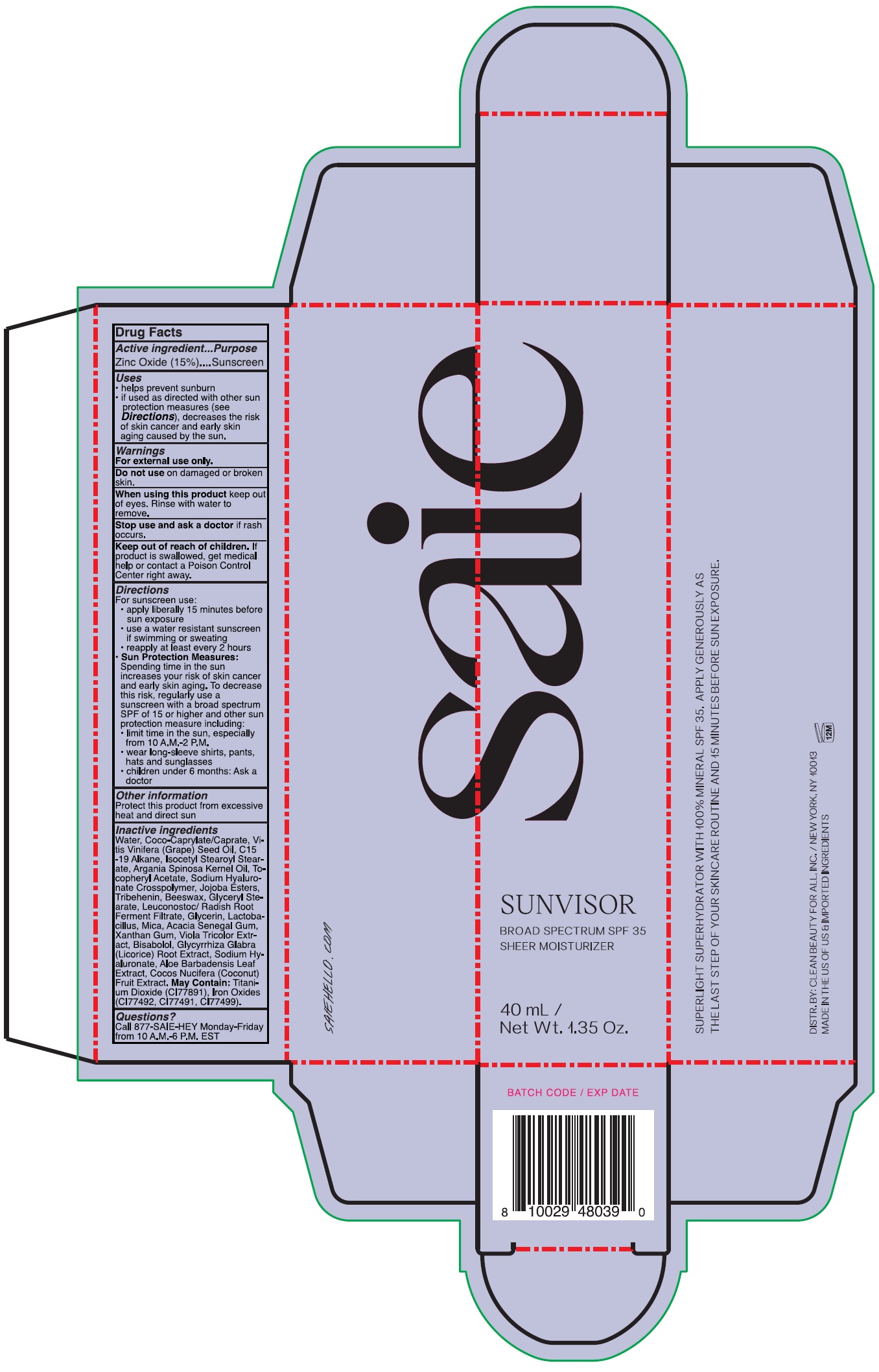 DRUG LABEL: Saie Sunvisor Broad Spectrum SPF 35 Sheer Moisturizer
NDC: 90086-011 | Form: LOTION
Manufacturer: Clean Beauty For All, Inc
Category: otc | Type: HUMAN OTC DRUG LABEL
Date: 20231212

ACTIVE INGREDIENTS: ZINC OXIDE 150 mg/1 mL
INACTIVE INGREDIENTS: WATER; COCOYL CAPRYLOCAPRATE; GRAPE SEED OIL; C15-19 ALKANE; ISOCETYL STEAROYL STEARATE; ARGAN OIL; .ALPHA.-TOCOPHEROL ACETATE; HYALURONATE SODIUM; TRIBEHENIN; YELLOW WAX; GLYCERYL MONOSTEARATE; LEUCONOSTOC/RADISH ROOT FERMENT FILTRATE; GLYCERIN; MICA; ACACIA; XANTHAN GUM; VIOLA TRICOLOR WHOLE; LEVOMENOL; GLYCYRRHIZA GLABRA; ALOE VERA LEAF; COCONUT; TITANIUM DIOXIDE

Saie Sunvisor Broad Spectrum SPF 35 Sheer Moisturizer

Active ingredient

Zinc Oxide (15%)

Purpose

Sunscreen

Uses

- helps prevent sunburn
- if used as directed with other sun protection measures (see), decreases the risk of skin cancer and early skin aging caused by the sun. Directions

Warnings

For external use only.

Do not use

on damaged or broken skin.

When using this product

keep out of eyes. Rinse with water to remove.

Stop use and ask a doctor

if rash occurs.

Keep out of reach of children.

If product is swallowed, get medical help or contact a Poison Control Center right away.

Directions

For sunscreen use: • apply liberally 15 minutes before sun exposure • use a water resistant sunscreen if swimming or sweating • reapply at least every 2 hours • Spending time in the sun increases your risk of skin cancer and early skin aging. To decrease this risk, regularly use a sunscreen with a broad spectrum SPF of 15 or higher and other sun protection measures including: • limit time in the sun, especially from 10 a.m. – 2 p.m. • wear long-sleeve shirts, pants, hats, and sunglasses • children under 6 months: Ask a doctor
Sun Protection Measures:

Other information

Protect this product from excessive heat and direct sun

Inactive ingredients

Water, Coco-Caprylate/Caprate, Vitis Vinifera (Grape) Seed Oil, C15-19 Alkane, Isocetyl Stearoyl Stearate, Argania Spinosa Kernel Oil, Tocopheryl Acetate, Sodium Hyaluronate Crosspolymer, Jojoba Esters, Tribehenin, Beeswax, Glyceryl Stearate, Leuconostoc/ Radih Root Ferment Filtrate, Glycerin, Lactobacillus, Mica, Acacia Senegal Gum, Xanthan Gum, Viola Tricolor Extract, Bisabolol, Glycyrrhiza Glabra (Licorice) Root Extract, Sodium Hyaluronate, Aloe Barbadensis Leaf Extract, Cocos Nucifera (Coconut) Fruit Extract. May Contain:Titanium Dioxide (CI77891), Iron Oxide (CI77492, CI77491, CI77499).

Questions?

Call 877-SAIE-HEY Monday-Friday from 10 A.M.-6 P.M EST